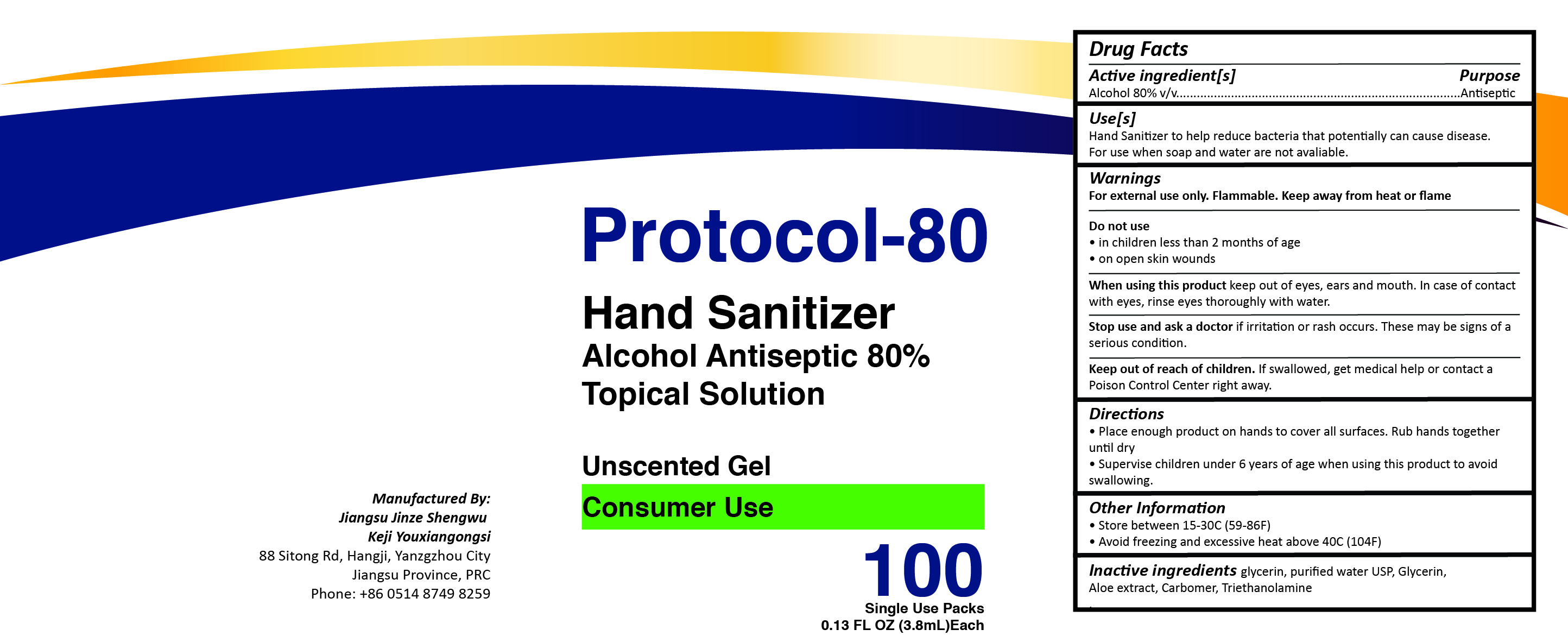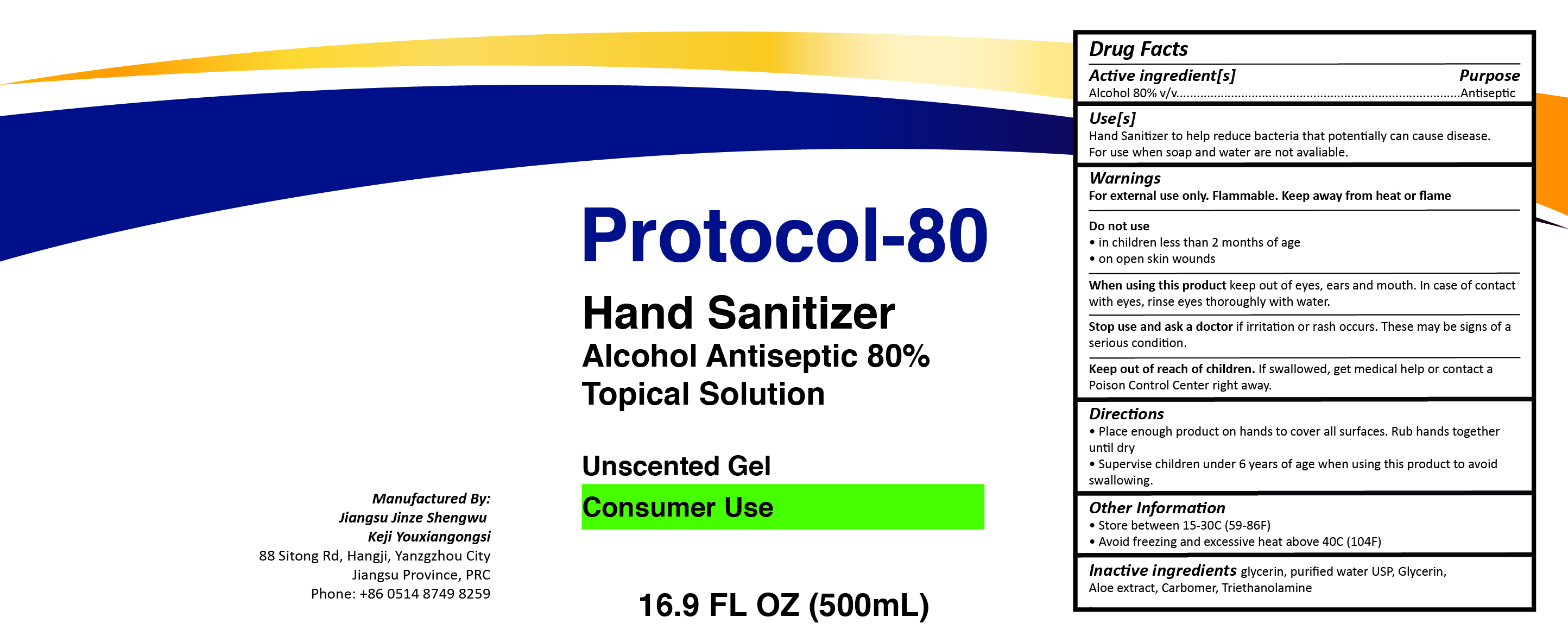 DRUG LABEL: Protocol-80 Hand Sanitizer
NDC: 74717-800 | Form: GEL
Manufacturer: Jiangsu Jinze Biotechnology Co., Ltd.
Category: otc | Type: HUMAN OTC DRUG LABEL
Date: 20200423

ACTIVE INGREDIENTS: ALCOHOL 80 mL/100 mL
INACTIVE INGREDIENTS: TROLAMINE 0.3 mL/100 mL; CARBOMER HOMOPOLYMER, UNSPECIFIED TYPE 0.35 mL/100 mL; ALOE 0.5 mL/100 mL; GLYCERIN 5 mL/100 mL; WATER 13.35 mL/100 mL

Protocol-80 Hand Sanitizer Gel

This is a hand sanitizer formulated to contain an 80% Alcohol Conetnt

Active Ingredient(s)

Alcohol 80% v/v. Purpose: Antiseptic

Purpose

Antiseptic, Hand Sanitizer

Use

Hand Sanitizer to help reduce bacteria that potentially can cause disease. For use when soap and water are not available.

Warnings

For external use only. Flammable. Keep away from heat or flame

Do not use

- in children less than 2 months of age
- on open skin wounds

When using this product keep out of eyes, ears, and mouth. In case of contact with eyes, rinse eyes thoroughly with water.
Stop use and ask a doctor if irritation or rash occurs. These may be signs of a serious condition.
Keep out of reach of children. If swallowed, get medical help or contact a Poison Control Center right away.

Stop use and ask a doctor if irritation or rash occurs. These may be signs of a serious condition.

Keep out of reach of children. If swallowed, get medical help or contact a Poison Control Center right away.

Directions

- Place enough product on hands to cover all surfaces. Rub hands together until dry.
- Supervise children under 6 years of age when using this product to avoid swallowing.

Other information

- Store between 15-30C (59-86F)
- Avoid freezing and excessive heat above 40C (104F)

Inactive ingredients

glycerin, hydrogen peroxide, purified water USP, Aloe extract, Carbomer, Triethanolamine

Package Label - Principal Display Panel

500 mL NDC: 74717-800-01

3.8 mL NDC: 74717-800-2